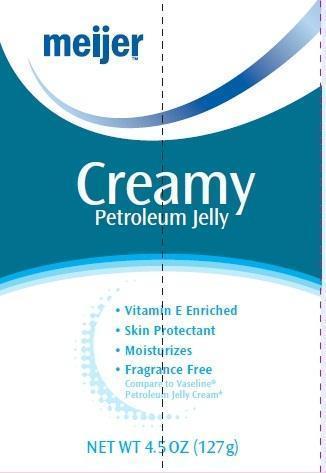 DRUG LABEL: Creamy Petroleum
NDC: 41250-070 | Form: JELLY
Manufacturer: Meijer Distribution, Inc
Category: otc | Type: HUMAN OTC DRUG LABEL
Date: 20131003

ACTIVE INGREDIENTS: PETROLATUM  .30 mg/100 g
INACTIVE INGREDIENTS: WATER; ALUMINUM STARCH OCTENYLSUCCINATE; ALKYL (C12-15) BENZOATE; MYRISTYL MYRISTATE; CETOSTEARYL ALCOHOL; GLYCERIN; MICROCRYSTALLINE WAX; POLYOXYL 20 CETOSTEARYL ETHER; TROLAMINE; CARBOMER HOMOPOLYMER TYPE C (ALLYL PENTAERYTHRITOL CROSSLINKED); METHYLPARABEN; DMDM HYDANTOIN; ETHYLENE BRASSYLATE; EDETATE DISODIUM; .ALPHA.-TOCOPHEROL ACETATE

Drug Facts

claims

Meijer Creamy Petroleum Jelly is specially formulated to moisturize and protect. Use Meijer Creamy Petroleum jelly to soften and smooth wherever dry skin occurs. This extra moisturizing product is formulated with pure petroleum jelly and blended into a pleasant, creamy base that also contains Vitamin E. Use on hands, elbows, knees and heals to smooth away dryness and leave a soft, supple feel. Also, excellent for moisturizing neck and facial skin.

Active ingredient

White Petrolatum, USP 30%

Purpose

Skin Protectant

Uses

- temporarily protects minor: - cuts -scrapes - burns
- temporarily protects and helps relieve chapped or cracked skin
- helps protect from the drying effects of wind and cold weather

Warnings for this product

For external use only

When using this product

do not get into eyes.

Stop use and ask a doctor if

- condition worsens
- symptoms last more than 7 days or clear up again within a few days

Do not use on

- deep or puncture wounds
- animal bites
- serious burns

Keep out of reach of children

If swallowed, get medical help or contact a Poison Control Center right away.

Directions

apply as needed

Inactive ingredients

water, aluminum starch octenylsuccinate, C12-15 alkyl benzoate, myristyl myristate, cetearyl alcohol, glycerin, microcrystalline wax, ceteareth-20, triethanolamine, carbomer, methylparaben, DMDM hydantoin, ethylene brassylate, disodium EDTA, tocopheryl acetate (vitamin E acetate).

Disclaimer

This product is not manufactured or distributed by UNILEVER, distributor of Vaseline

Adverse Reactions

DIST. BY MEIJER DISTRIBUTION, INC.

2929 WALKER AVE NW

GRAND RAPIDS, MI 49544

www.meijer.com

Principal Display Panel

meijer

Creamy

Petroleum Jelly

- Vitamin E Enriched
- Skin Protectant
- Moisturizes
- Fragrance Free

Compare to Vaseline Petroleum Jelly Cream

NET WT 4.5 OZ (127 g)